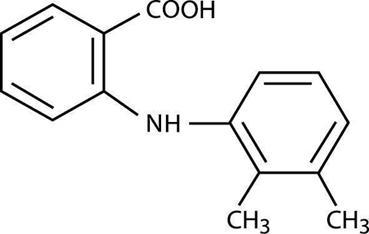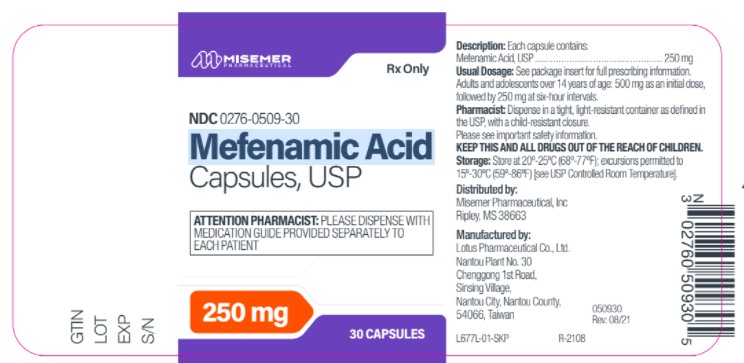 DRUG LABEL: Mefenamic Acid
NDC: 0276-0509 | Form: CAPSULE
Manufacturer: Misemer Pharmaceuticals, Inc
Category: prescription | Type: HUMAN PRESCRIPTION DRUG LABEL
Date: 20260226

ACTIVE INGREDIENTS: MEFENAMIC ACID 250 mg/1 1
INACTIVE INGREDIENTS: LACTOSE MONOHYDRATE; D&C YELLOW NO. 10; TITANIUM DIOXIDE; GELATIN; FD&C YELLOW NO. 6; SHELLAC; PROPYLENE GLYCOL; FERRIC OXIDE YELLOW; FD&C BLUE NO. 1; DIMETHICONE

Mefenamic Acid

BOXED WARNING

Cardiovascular Risk

- NSAIDs may cause an increased risk of serious cardiovascular thrombotic events, myocardial infarction, and stroke, which can be fatal. This risk may increase with duration of use. Patients with cardiovascular disease or risk factors for cardiovascular disease may be at greater risk (See WARNINGS).

- Mefenamic acid is contraindicated for the treatment of peri-operative pain in the setting of coronary artery bypass graft (CABG) surgery (See WARNINGS).

Gastrointestinal Risk

- NSAIDs cause an increased risk of serious gastrointestinal adverse events including bleeding, ulceration, and perforation of the stomach or intestines, which can be fatal.

These events can occur at any time during use and without warning symptoms. Elderly patients are at greater risk for serious gastrointestinal events (See WARNINGS).

DESCRIPTION

Mefenamic acid is a member of the fenamate group of nonsteroidal anti-inflammatory drugs (NSAIDs). Each green-banded, yellow capsule contains 250 mg of mefenamic acid for oral administration. Mefenamic acid is a white to greyish-white, odorless, microcrystalline powder with a melting point of 230°-231°C and water solubility of 0.004% at pH 7.1. The chemical name is N-2,3-xylylanthranilic acid. The molecular weight is 241.29. Its molecular formula is C15H15NO2 and the structural formula of mefenamic acid is:

Each capsule also contains lactose monohydrate. The capsule shell and band contain dimethicone, D&C yellow No. 10, FD&C blue No. 1 aluminum lake, FD&C yellow No. 6, gelatin, propylene glycol, shellac, titanium dioxide and yellow iron oxide.

CLINICAL PHARMACOLOGY

Pharmacodynamics

Mefenamic acid is a non-steroidal anti-inflammatory drug (NSAID) that exhibits anti-inflammatory, analgesic, and antipyretic activities in animal models. The mechanism of action of mefenamic acid, like that of other NSAIDs, is not completely understood but may be related to prostaglandin synthetase inhibition.

Pharmacokinetics

Absorption

Mefenamic acid is rapidly absorbed after oral administration. In two 500-mg single oral dose studies, the mean extent of absorption was 30.5 mcg/hr/mL (17%CV).^1,2 The bioavailability of the capsule relative to an IV dose or an oral solution has not been studied. Following a single 1-gram oral dose, mean peak plasma levels ranging from 10-20 mcg/mL^3 have been reported. Peak plasma levels are attained in 2 to 4 hours and the elimination half-life approximates 2 hours. Following multiple doses, plasma levels are proportional to dose with no evidence of drug accumulation. In a multiple dose trial of normal adult subjects (n=6) receiving 1-gram doses of mefenamic acid four times daily, steady-state concentrations of 20 mcg/mL were reached on the second day of administration, consistent with the short half-life.

The effect of food on the rate and extent of absorption of mefenamic acid has not been studied. Concomitant ingestion of antacids containing magnesium hydroxide has been shown to significantly increase the rate and extent of mefenamic acid absorption (see PRECAUTIONS, Drug Interactions).^1

Distribution

Mefenamic acid has been reported as being greater than 90% bound to albumin.^9 The relationship of unbound fraction to drug concentration has not been studied. The apparent volume of distribution (Vzss/F) estimated following a 500-mg oral dose of mefenamic acid was 1.06 L/kg.^2

Based on its physical and chemical properties, mefenamic acid is expected to be excreted in human breast milk.

Metabolism

Mefenamic acid is metabolized by cytochrome P450 enzyme CYP2C9 to 3-hydroxymethyl mefenamic acid (Metabolite I). Further oxidation to a 3-carboxymefenamic acid (Metabolite II) may occur.^10 The activity of these metabolites has not been studied. The metabolites may undergo glucuronidation and mefenamic acid is also glucuronidated directly. A peak plasma level approximating 20 mcg/mL was observed at 3 hours for the hydroxy metabolite and its glucuronide (n=6) after a single 1-gram dose. Similarly, a peak plasma level of 8 mcg/mL was observed at 6-8 hours for the carboxy metabolite and its glucuronide.^3

Excretion

Approximately fifty-two percent of a mefenamic acid dose is excreted into the urine primarily as glucuronides of mefenamic acid (6%), 3-hydroxymefenamic acid (25%) and 3-carboxymefenamic acid (21%). The fecal route of elimination accounts for up to 20% of the dose, mainly in the form of unconjugated 3-carboxymefenamic acid.^3

The elimination half-life of mefenamic acid is approximately two hours. Half-lives of metabolites I and II have not been precisely reported, but appear to be longer than the parent compound.^3 The metabolites may accumulate in patients with renal or hepatic failure. The mefenamic acid glucuronide may bind irreversibly to plasma proteins. Because both renal and hepatic excretion are significant pathways of elimination, dosage adjustments in patients with renal or hepatic dysfunction may be necessary. Mefenamic acid should not be administered to patients with preexisting renal disease or in patients with significantly impaired renal function.

TABLE 1. Pharmacokinetic Parameter Estimates for Mefenamic Acid
PK Parameters | Normal Healthy Adults (18-45 yr)
 | Value | CV
Tmax(hr) | 2 | 66
Oral clearance (L/hr) | 21.23 | 38
Apparent volume of distribution; Vz/F (L/kg) | 1.06 | 60
Half-life; t ½ (hrs) | 2 to 4 | NA

Special Populations

Pediatric

Mefenamic acid has not been adequately investigated in pediatric patients less than 14 years of age.

A study in 17 preterm infants administered 2 mg/kg indicated that the half-life was about five times as long as adults, consistent with the low activity of metabolic enzymes in newborn infants. The mean Cmax in this study was 4 mcg/mL (range 2.9-6.1). The mean time to maximum concentration (Tmax) was 8 hours (range 2-18 hrs).^11

Race

Pharmacokinetic differences due to race have not been identified.

Hepatic Insufficiency

Mefenamic acid pharmacokinetics have not been studied in patients with hepatic dysfunction. As hepatic metabolism is a significant pathway of mefenamic acid elimination, patients with acute and chronic hepatic disease may require reduced doses of mefenamic acid compared to patients with normal hepatic function.

Renal Insufficiency

Mefenamic acid pharmacokinetics have not been investigated in subjects with renal insufficiency. Given that mefenamic acid, its metabolites and conjugates are primarily excreted by the kidneys, the potential exists for mefenamic acid metabolites to accumulate. Mefenamic acid should not be administered to patients with pre-existing renal disease or in patients with significantly impaired renal function.

CLINICAL STUDIES

In controlled, double-blind, clinical trials, mefenamic acid was evaluated for the treatment of primary spasmodic dysmenorrhea. The parameters used in determining efficacy included pain assessment by both patient and investigator; the need for concurrent analgesic medication; and evaluation of change in frequency and severity of symptoms characteristic of spasmodic dysmenorrhea. Patients received either mefenamic acid, 500 mg (2 capsules) as an initial dose of 250 mg every 6 hours, or placebo at onset of bleeding or of pain, whichever began first. After three menstrual cycles, patients were crossed over to the alternate treatment for an additional three cycles. Mefenamic acid was significantly superior to placebo in all parameters, and both treatments (drug and placebo) were equally tolerated.

INDICATIONS AND USAGE

Carefully consider the potential benefits and risks of mefenamic acid and other treatment options before deciding to use mefenamic acid. Use the lowest effective dose for the shortest duration consistent with individual patient treatment goals (see WARNINGS).

Mefenamic acid is indicated:

- For relief of mild to moderate pain in patients ≥14 years of age, when therapy will not exceed one week (7 days).
- For treatment of primary dysmenorrhea.

CONTRAINDICATIONS

Mefenamic acid is contraindicated in patients with known hypersensitivity to mefenamic acid.

Mefenamic acid should not be given to patients who have experienced asthma, urticaria, or allergic-type reactions after taking aspirin or other NSAIDs. Severe, rarely fatal, anaphylactic-like reactions to NSAIDs have been reported in such patients (see WARNINGS - Anaphylactoid Reactions, and PRECAUTIONS - Preexisting Asthma).

Mefenamic acid is contraindicated for the treatment of peri-operative pain in the setting of coronary artery bypass graft (CABG) surgery (see WARNINGS).

Mefenamic acid is contraindicated in patients with acute active ulceration or chronic inflammation of either the upper or lower gastrointestinal tract.

Mefenamic acid should not be used in patients with pre-existing renal disease.

WARNINGS

CARDIOVASCULAR EFFECTS

Cardiovascular Thrombotic Events

Clinical trials of several COX-2 selective and nonselective NSAIDs of up to three years duration have shown an increased risk of serious cardiovascular (CV) thrombotic events, myocardial infarction, and stroke, which can be fatal. All NSAIDs, both COX-2 selective and nonselective, may have a similar risk. Patients with known CV disease or risk factors for CV disease may be at greater risk. To minimize the potential risk for an adverse CV event in patients treated with an NSAID, the lowest effective dose should be used for the shortest duration possible. Physicians and patients should remain alert for the development of such events, even in the absence of previous CV symptoms. Patients should be informed about the signs and/or symptoms of serious CV events and the steps to take if they occur. There is no consistent evidence that concurrent use of aspirin mitigates the increased risk of serious CV thrombotic events associated with NSAID use. The concurrent use of aspirin and an NSAID does increase the risk of serious GI events (see GI WARNINGS).

Two large, controlled, clinical trials of a COX-2 selective NSAID for the treatment of pain in the first 10-14 days following CABG surgery found an increased incidence of myocardial infarction and stroke (see CONTRAINDICATIONS).

Hypertension

NSAIDs, including mefenamic acid, can lead to onset of new hypertension or worsening of preexisting hypertension, either of which may contribute to the increased incidence of CV events. Patients taking thiazides or loop diuretics may have impaired response to these therapies when taking NSAIDs. NSAIDS, including mefenamic acid, should be used with caution in patients with hypertension. Blood pressure (BP) should be monitored closely during the initiation of NSAID treatment and throughout the course of therapy.

Congestive Heart Failure and Edema

Fluid retention and edema have been observed in some patients taking NSAIDs. Mefenamic acid should be used with caution in patients with fluid retention or heart failure.

Gastrointestinal Effects - Risk of Ulceration, Bleeding, and Perforation

NSAIDs, including mefenamic acid, can cause serious gastrointestinal (GI) adverse events including inflammation, bleeding, ulceration, and perforation of the stomach, small intestine, or large intestine, which can be fatal. These serious adverse events can occur at any time, with or without warning symptoms, in patients treated with NSAIDs. Only one in five patients, who develop a serious upper GI adverse event on NSAID therapy, is symptomatic. Upper GI ulcers, gross bleeding, or perforation caused by NSAIDs occur in approximately 1% of patients treated for 3-6 months, and in about 2-4% of patients treated for one year. These trends continue with longer duration of use, increasing the likelihood of developing a serious GI event at sometime during the course of therapy. However, even short-term therapy is not without risk.

NSAIDs should be prescribed with extreme caution in those with a prior history of ulcer disease or gastrointestinal bleeding. Patients with a prior history of peptic ulcer disease and/or gastrointestinal bleeding who use NSAIDs have a greater than 10-fold increased risk for developing a GI bleed compared to patients with neither of these risk factors. Other factors that increase the risk for GI bleeding in patients treated with NSAIDs include concomitant use of oral corticosteroids or anti-coagulants, longer duration of NSAID therapy, smoking, use of alcohol, older age, and poor general health status. Most spontaneous reports of fatal GI events are in elderly or debilitated patients and therefore, special care should be taken in treating this population.

To minimize the potential risk for an adverse GI event in patients treated with an NSAID, the lowest effective dose should be used for the shortest possible duration. Patients and physicians should remain alert for signs and symptoms of GI ulceration and bleeding during NSAID therapy and promptly initiate additional evaluation and treatment if a serious GI adverse event is suspected. This should include discontinuation of the NSAID until a serious GI adverse event is ruled out. For high risk patients, alternate therapies that do not involve NSAIDs should be considered.

Renal Effects

Long-term administration of NSAIDs have resulted in renal papillary necrosis and other renal injury. Renal toxicity has also been seen in patients in whom renal prostaglandins have a compensatory role in the maintenance of renal perfusion. In these patients, administration of a nonsteroidal anti-inflammatory drug may cause a dose-dependent reduction in prostaglandin formation and, secondarily, in renal blood flow, which may precipitate overt renal decompensation. Patients at greatest risk of this reaction are those with impaired renal function, heart failure, liver dysfunction, those taking diuretics and ACE-inhibitors, and the elderly. Discontinuation of NSAID therapy is usually followed by recovery to the pretreatment state.

Advanced Renal Disease

No information is available for controlled studies regarding the use of mefenamic acid in patients with advanced renal disease. Therefore, treatment with mefenamic acid is not recommended in these patients with advanced renal disease (see CONTRAINDICATIONS).

Anaphylactoid Reactions

As with other NSAIDs, anaphylactoid reactions may occur in patients without known prior exposure to mefenamic acid. Mefenamic acid should not be given to patients with the aspirin triad. This symptom complex typically occurs in asthmatic patients who experience rhinitis with or without nasal polyps, or who exhibit severe, potentially fatal bronchospasm after taking aspirin or other NSAIDs (see CONTRAINDICATIONS and PRECAUTIONS - Preexisting Asthma). Emergency help should be sought in cases where an anaphylactoid reaction occurs.

Skin Reactions

NSAIDs, including mefenamic acid, can cause serious skin adverse events such as exfoliative dermatitis, Stevens-Johnson Syndrome (SJS), and toxic epidermal necrolysis (TEN), which can be fatal. These serious events may occur without warning. Patients should be informed about the signs and symptoms of serious skin manifestations and use of the drug should be discontinued at the first appearance of skin rash or any other sign of hypersensitivity.

Pregnancy

In late pregnancy, as with other NSAIDs, mefenamic acid should be avoided because it may cause premature closure of the ductus arteriosus.

PRECAUTIONS

General

Mefenamic acid cannot be expected to substitute for corticosteroids or to treat corticosteroid insufficiency. Abrupt discontinuation of corticosteroids may lead to disease exacerbation. Patients on prolonged corticosteroid therapy should have their therapy tapered slowly if a decision is made to discontinue corticosteroids.

The pharmacological activity of mefenamic acid in reducing fever and inflammation may diminish the utility of these diagnostic signs in detecting complications of presumed noninfectious, painful conditions.

Hepatic Effects

Borderline elevations of one or more liver tests may occur in up to 15% of patients taking NSAIDs, including mefenamic acid. These laboratory abnormalities may progress, may remain unchanged, or may be transient with continuing therapy. Notable elevations of ALT or AST (approximately three or more times the upper limit of normal) have been reported in approximately 1% of patients in clinical trials with NSAIDs. In addition, rare cases of severe hepatic reactions, including jaundice and fatal fulminant hepatitis, liver necrosis and hepatic failure, some of them with fatal outcomes, have been reported.

A patient with symptoms and/or signs suggesting liver dysfunction, or in whom an abnormal liver test has occurred, should be evaluated for evidence of the development of a more severe hepatic reaction while

on therapy with mefenamic acid. If clinical signs and symptoms consistent with liver disease develop, or if systemic manifestations occur (e.g., eosinophilia, rash, etc.), mefenamic acid should be discontinued.

Hematological Effects

Anemia is sometimes seen in patients receiving NSAIDs, including mefenamic acid. This may be due to fluid retention, GI blood loss, or an incompletely described effect upon erythropoiesis. Patients on long-term treatment with NSAIDs, including mefenamic acid, should have their hemoglobin or hematocrit checked if they exhibit any signs or symptoms of anemia. NSAIDs inhibit platelet aggregation and have been shown to prolong bleeding time in some patients. Unlike aspirin, their effect on platelet function is quantitatively less, of shorter duration, and reversible. Patients receiving mefenamic acid who may be adversely affected by alterations in platelet function, such as those with coagulation disorders or patients receiving anticoagulants, should be carefully monitored.

Pre-existing Asthma

Patients with asthma may have aspirin-sensitive asthma. The use of aspirin in patients with aspirin-sensitive asthma has been associated with severe bronchospasm which can be fatal. Since cross reactivity, including bronchospasm, between aspirin and other nonsteroidal anti-inflammatory drugs has been reported in such aspirin-sensitive patients, mefenamic acid should not be administered to patients with this form of aspirin sensitivity and should be used with caution in patients with pre-existing asthma.

Information for Patients

Patients should be informed of the following information before initiating therapy with an NSAID and periodically during the course of ongoing therapy. Patients should also be encouraged to read the NSAID Medication Guide that accompanies each prescription dispensed.

1. Mefenamic acid, like other NSAIDs, may cause serious CV side effects, such as MI or stroke, which may result in hospitalization and even death. Although serious CV events can occur without warning symptoms, patients should be alert for the signs and symptoms of chest pain, shortness of breath, weakness, slurring of speech, and should ask for medical advice when observing any indicative sign or symptoms. Patients should be apprised of the importance of this follow-up (see WARNINGS, Cardiovascular Effects).
2. Mefenamic acid, like other NSAIDs, can cause GI discomfort and, rarely, serious GI side effects, such as ulcers and bleeding, which may result in hospitalizations and even death. Although serious GI tract ulcerations and bleeding can occur without warning symptoms, patients should be alert for the signs and symptoms of ulceration and bleeding, and should ask for medical advice when observing any indicative sign or symptoms including epigastric pain, dyspepsia, melena, and hematemesis. Patients should be apprised of the importance of this follow-up (see WARNINGS, Gastrointestinal Effects: Risk of Ulceration, Bleeding, and Perforation).
3. Mefenamic acid, like other NSAIDs, can cause serious skin side effects such as exfoliative dermatitis, SJS, and TEN, which may result in hospitalizations and even death. Although serious skin reactions may occur without warning, patients should be alert for the signs and symptoms of skin rash and blisters, fever, or other signs of hypersensitivity such as itching, and should ask for medical advice when observing any indicative signs or symptoms. Patients should be advised to stop the drug immediately if they develop any type of rash and contact their physicians as soon as possible.
4. Patients should promptly report signs or symptoms of unexplained weight gain or edema to their physicians.
5. Patients should be informed of the warning signs and symptoms of hepatotoxicity (e.g. nausea, fatigue, lethargy, pruritus, jaundice, right upper quadrant tenderness, and "flu-like" symptoms). If these occur, patients should be instructed to stop therapy and seek immediate medical therapy.
6. Patients should be informed of the signs of an anaphylactoid reaction (e.g. difficulty breathing, swelling of the face or throat). If these occur, patients should be instructed to seek immediate emergency help (see WARNINGS).
7. In late pregnancy, as with other NSAIDs, mefenamic acid should be avoided because it may cause premature closure of the ductus arteriosus.

Laboratory Tests

Because serious GI tract ulcerations and bleeding can occur without warning symptoms, physicians should monitor for signs or symptoms of GI bleeding. Patients on long-term treatment with NSAIDs should have their CBC and a chemistry profile checked periodically. If clinical signs and symptoms consistent with liver or renal disease develop, systemic manifestations occur (e.g., eosinophilia, rash, etc.) or if abnormal liver tests persist or worsen, mefenamic acid should be discontinued.

Drug Interactions

A number of compounds are inhibitors of CYP2C9. Drug interactions studies of mefenamic acid and these compounds have not been conducted. The possibility of altered safety and efficacy should be considered when mefenamic acid is used concomitantly with these drugs.

ACE-inhibitors

Reports suggest that NSAIDs may diminish the antihypertensive effect of ACE-inhibitors. This interaction should be given consideration in patients taking NSAIDs concomitantly with ACE-inhibitors.

Aspirin

When mefenamic acid is administered with aspirin, its protein binding is reduced, although the clearance of free mefenamic acid is not altered. The clinical significance of this interaction is not known; however, as with other NSAIDs, concomitant administration of MEFENAMIC ACID and aspirin is not generally recommended because of the potential of increased adverse effects.

Diuretics

Clinical studies, as well as post marketing observations, have shown that mefenamic acid can reduce the natriuretic effect-of furosemide and thiazides in some patients. This response has been attributed to inhibition of renal prostaglandin synthesis. During concomitant therapy of NSAIDs, the patient should be observed closely for signs of renal failure (see PRECAUTIONS, Renal Effects), as well as to assure diuretic efficacy.

Lithium

NSAIDs have produced an elevation of plasma lithium levels and a reduction in renal lithium clearance. The mean minimum lithium concentration increased 15% and the renal clearance decreased by approximately 20%. These effects have been attributed to inhibition of renal prostaglandin synthesis by the NSAID. Thus, when NSAIDs and lithium are administered concurrently, subjects should be observed carefully for signs of lithium toxicity.

Methotrexate

NSAIDs have been reported to competitively inhibit methotrexate accumulation in rabbit kidney slices. This may indicate that they could enhance the toxicity of methotrexate. Caution should be used when NSAIDs are administered concomitantly with methotrexate.

Warfarin

The effects of warfarin and NSAIDs on GI bleeding are synergistic, such that users of both drugs together have a risk of serious GI bleeding higher than users of either drug alone.

Antacids

In a single dose study (n=6), ingestion of an antacid containing 1.7-gram of magnesium hydroxide with 500-mg of mefenamic acid increased the Cmax and AUC of mefenamic acid by 125% and 36%, respectively.^1

Drug/Laboratory Test Interactions

Mefenamic acid may prolong prothrombin time.^4 Therefore, when the drug is administered to patients receiving oral anticoagulant drugs, frequent monitoring of prothrombin time is necessary.

A false-positive reaction for urinary bile, using the diazo tablet test, may result after mefenamic acid administration. If biliuria is suspected, other diagnostic procedures, such as the Harrison spot test, should be performed.

Pregnancy

Teratogenic Effects:

Pregnancy Category C.

Reproductive studies conducted in rats and rabbits have not demonstrated evidence of developmental abnormalities. However, animal reproduction studies are not always predictive of human response. There are no adequate or well controlled studies in pregnant women. Mefenamic acid should be used in pregnancy only if the potential benefit justifies the potential risk to the fetus.

Nonteratogenic Effects:

Because of the known effects of nonsteroidal anti-inflammatory drugs on the fetal cardiovascular system (closure of ductus arteriosus), use during pregnancy (particularly late pregnancy) should be avoided.

Labor and Delivery

In rat studies with NSAIDs, as with other drugs known to inhibit prostaglandin synthesis, an increased incidence of dystocia, delayed parturition, and decreased pup survival occurred. The effects of mefenamic acid on labor and delivery in pregnant women are unknown.

Nursing Mothers

Trace amounts of mefenamic acid may be present in breast milk and transmitted to the nursing infant.^7 Because of the potential for serious adverse reactions in nursing infants from mefenamic acid, a decision should be made whether to discontinue nursing or to discontinue the drug, taking into account the importance of the drug to the mother.

Pediatric Use

Safety and effectiveness in pediatric patients below the age of 14 have not been established.

Geriatric Use

Clinical studies of mefenamic acid did not include sufficient numbers of subjects aged 65 and over to determine whether they respond differently from younger subjects. As with any NSAIDs, caution should be exercised in treating the elderly (65 years and older).

This drug is known to be substantially excreted by the kidney, and the risk of toxic reactions to this drug may be greater in patients with impaired renal function. Because elderly patients are more likely to have decreased renal function, care should be taken in dose selection, and it may be useful to monitor renal function (see CLINICAL PHARMACOLOGY and ADVERSE EVENTS).

ADVERSE REACTIONS

In patients taking mefenamic acid or other NSAIDs, the most frequently reported adverse experiences occurring in approximately 1-10% of patients are:

Gastrointestinal experiences including - abdominal pain, constipation, diarrhea, dyspepsia, flatulence, gross bleeding/perforation, heartburn, nausea, GI ulcers (gastric/duodenal), vomiting, abnormal renal function, anemia, dizziness, edema, elevated liver enzymes, headaches, increased bleeding time, pruritus, rashes, tinnitus.

Additional adverse experiences reported occasionally and listed here by body system include:

Body as a whole - fever, infection, sepsis

Cardiovascular system - congestive heart failure, hypertension, tachycardia, syncope

Digestive system - dry mouth, esophagitis, gastric/peptic ulcers, gastritis, gastrointestinal bleeding, glossitis, hematemesis, hepatitis, jaundice

Hemic and lymphatic system - ecchymosis, eosinophilia, leukopenia, melena, purpura, rectal bleeding, stomatitis, thrombocytopenia

Metabolic and nutritional - weight changes

Nervous system - anxiety, asthenia, confusion, depression, dream abnormalities, drowsiness; insomnia, malaise, nervousness, paresthesia, somnolence, tremors, vertigo

Respiratory system - asthma, dyspnea

Skin and appendages - alopecia, photosensitivity, pruritus, sweat

Special senses - blurred vision

Urogenital system - cystitis, dysuria, hematuria, interstitial nephritis, oliguria/polyuria, proteinuria, renal failure

Other adverse reactions, which occur rarely are:

Body as a whole - anaphylactoid reactions, appetite changes, death

Cardiovascular system - arrhythmia, hypotension, myocardial infarction, palpitations, vasculitis

Digestive system - eructation, liver failure, pancreatitis

Hemic and lymphatic system - agranulocytosis, hemolytic anemia, aplastic anemia, lymphadenopathy, pancytopenia

Metabolic and nutritional – hyperglycemia

Nervous system - convulsions, coma, hallucinations, meningitis

Respiratory - respiratory depression, pneumonia

Skin and appendages - angioedema, toxic epidermal necrosis, erythema multiforme, exfoliative dermatitis, Stevens-Johnson syndrome, urticaria

Special senses - conjunctivitis, hearing impairment

OVERDOSAGE

Symptoms following acute NSAIDs overdoses are usually limited to lethargy, drowsiness, nausea, vomiting, and epigastric pain, which are generally reversible with supportive care. Gastrointestinal bleeding can occur. Hypertension, acute renal failure, respiratory depression and coma may occur, but are rare. Anaphylactoid reactions have been reported with therapeutic ingestion of NSAIDs, and may occur following an overdose.

Patients should be managed by symptomatic and supportive care following an NSAID overdose. There are no specific antidotes. Emesis and/or activated charcoal (60 to 100 g in adults, 1 to 2 g/kg in children) and/or osmotic cathartic may be indicated in patients seen within 4 hours of ingestion with symptoms or following a large overdose (5 to 10 times the usual dose). Forced diuresis, alkalinization of urine, hemodialysis, or hemoperfusion may not be useful due to high protein binding.

DOSAGE AND ADMINISTRATION

Carefully consider the potential benefits and risks of mefenamic acid and other treatment options before deciding to use mefenamic acid. Use the lowest effective dose for the shortest duration consistent with individual patient treatment goals (see WARNINGS).

After observing the response to initial therapy with mefenamic acid, the dose and frequency should be adjusted to suit an individual patient's needs.

For the relief of acute pain in adults and adolescents ≥14 years of age, the recommended dose is 500 mg as an initial dose followed by 250 mg every 6 hours as needed, usually not to exceed one week.^4

For the treatment of primary dysmenorrhea, the recommended dose is 500 mg as an initial dose followed by 250 mg every 6 hours, given orally, starting with the onset of bleeding and associated symptoms. Clinical studies indicate that effective treatment can be initiated with the start of menses and should not be necessary for more than 2 to 3 days.^5

HOW SUPPLIED

Mefenamic acid is available as 250 mg green-banded, yellow capsules, imprinted with "BP" on the cap and "629" on the body in green ink. Bottles of 30, NDC# 0276-0509-30.

Dispense in a tight container as defined in the USP.

Storage

Store at 20°-25°C (68°-77°F); excursions permitted to 15°-30°C (59°-86°F) [See USP Controlled Room Temperature].

Medication Guide

Mefenamic (me-fe-NAM-ik) Acid Capsules USP

Rx only

Medication Guide for Nonsteroidal Anti-inflammatory Drugs (NSAIDS)

What is the most important information I should know about medicines called Nonsteroidal Anti-inflammatory Drugs (NSAIDs)?

NSAID can cause serious side effects, including:

Increase risk of a heart attack or stroke that can lead to death. This risk may happen early in treatment and may increase:

with increasing doses of NSAIDs
with longer use of NSAIDs

Do not take NSAIDs right before or after a heart surgery called a "coronary artery bypass graft (CABG)". Avoid taking NSAIDs after a recent heart attack, unless your healthcare provider tells you to. You may have an increased risk of another heart attack if you take NSAIDs after a recent heart attack.

Increase risk of bleeding, ulcers and tears (perforation) of the esophagus (tube leading from the mouth to the stomach), stomach and intestines:

anytime during use
without warning symptoms
that may cause death

The risk of getting an ulcer or bleeding increases with:

past history of stomach ulcers, or stomach or intestinal bleeding with use of NSAIDs
taking medicines called "corticosteroids", "anticoagulants", "SSRIs", or "SNRIs"
increasing doses of NSAIDs
longer use of NSAIDs
smoking
drinking alcohol
older age
poor health
advanced liver disease
bleeding problems

NSAID should only be used:

exactly as prescribed
at the lowest dose possible for your treatment
or the shortest time needed

What are NSAIDs?

NSAIDs are used to treat pain and redness, swelling, and heat (inflammation) from medical conditions such as different types of arthritis, menstrual cramps, and other types of short-term pain.

Who should not take NSAIDs?

Do not take NSAIDs:

if you have had an asthma attack, hives, or other allergic reaction with aspirin or any other NSAIDs.
right before or after heart bypass surgery.

Before taking NSAIDs, tell our healthcare provider about all of your medical conditions, including if you:

have liver or kidney problems
have high blood pressure
have asthma
are pregnant or plan to become pregnant. Taking NSAIDs at about 20 weeks of pregnancy or later may harm your unborn baby. If you need to take NSAIDs for more than 2 days when you are between 20 and 30 weeks of pregnancy, your healthcare provider may need to monitor the amount of fluid in your womb around your baby. You should not take NSAIDs after about 30 weeks of pregnancy
are breastfeeding or plan to breastfeed

Tell your healthcare provider about all of the medicines you take, including prescription or over-the-counter medicines, vitamins, or herbal supplements. NSAIDs and some other medicines can interact with each other and cause serious side effects. Do not start taking any new medicine without talking to your healthcare provider first.

What are the possible side effects of NSAIDs?

NSAIDs can cause serious side effects, including:

See "What is the most important information I should know about medicines called Nonsteroidal Anti-inflammatory Drugs (NSAIDs)?

new or worse high blood pressure
heart failure
liver problems including liver failure
kidney problem including kidney failure
low red blood cells (anemia)
life-threatening skin reactions
life-threatening allergic reactions
Other side effects if NSAIDs include: stomach pain, constipation, diarrhea, gas, heartburn, nausea, vomiting, and dizziness.

Get emergency help right away if you get any of the following symptoms:

shortness of breath or trouble breathing
chest pain
weakness in one part or side of your body
slurred speech
swelling of the face or throat

Stop taking your NSAID and call your healthcare provider right away if you get any of the following symptoms:

nausea
more tired or weaker than usual
diarrhea
itching
your skin or eyes look yellow
indigestion or stomach pain
flu-like symptoms
vomit blood
there is blood in the bowel movement or it is black and sticky like tar
unusual weight gain
skin rash or blisters with fever
swelling of the arms, legs, hands, and feet

If you take too much of your NSAID, call your healthcare provider or get medical help right away.

These are not all of the possible side effects of NSAIDs. For more information, ask your healthcare provider or pharmacist about NSAIDs.

Call your doctor for medical advice about side effects. You may report side effects to FDA at 1-800-FDA-1088 or Lupin Pharmaceuticals, Inc at 1-800-399-2561.

Other information about NSAIDs

Aspirin is an NSAID medicine but it does not increase the chance of a heart attack.
Aspirin can cause bleeding in the brain, stomach, and intestines. Aspirin can also cause ulcers in the stomach and intestines.
Some NSAIDs are sold in lower doses without a prescription (over-the-counter). Talk to your healthcare provider before using over-the-counter NSAID for more than 10 days.

General information about the safe and effective use of NSAIDs

Medicines are sometimes prescribed for purposes other than those listed in a Medication Guide. Do not use NSAIDs for a condition for which it was not prescribed. Do not give NSAIDs to other people, even if they have the same symptoms that you have. It may harm them.

If you would like more information about NSAIDs, talk with your healthcare provider. You can ask your pharmacist or healthcare provider for information about NSAIDs that is written for health professionals.

This Medication Guide has been approved by the U.S. Food and Drug Administration.